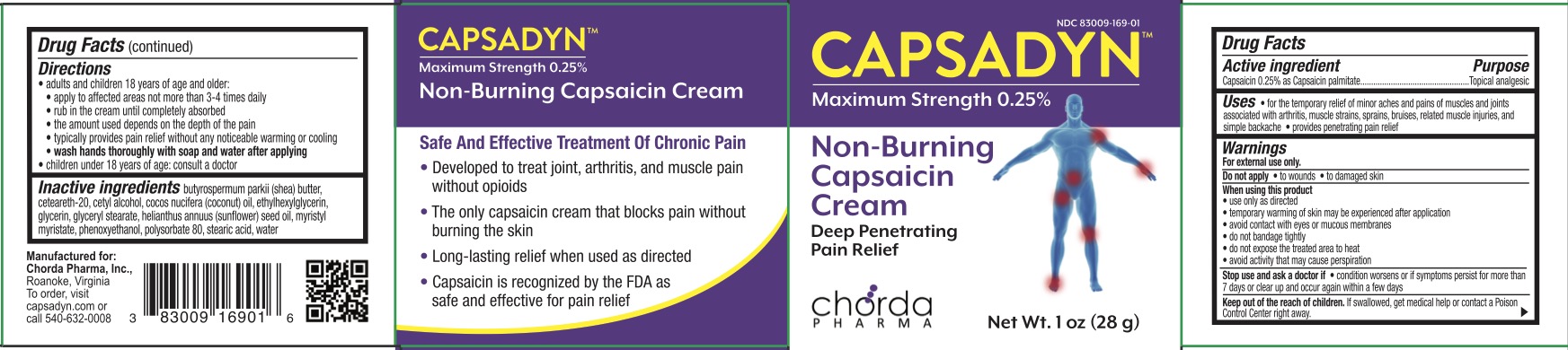 DRUG LABEL: Capsadyn
NDC: 83009-169 | Form: CREAM
Manufacturer: Chorda Pharma, Inc
Category: otc | Type: HUMAN OTC DRUG LABEL
Date: 20231011

ACTIVE INGREDIENTS: CAPSAICIN 0.25 g/100 g
INACTIVE INGREDIENTS: POLYSORBATE 80; PHENOXYETHANOL; STEARIC ACID; COCONUT OIL; ETHYLHEXYLGLYCERIN; GLYCERYL MONOSTEARATE; POLYOXYL 20 CETOSTEARYL ETHER; GLYCERIN; WATER; MYRISTYL MYRISTATE; SHEA BUTTER; SUNFLOWER OIL

Capsadyn

PURPOSE

Topical analgesic

ACTIVE INGREDIENT

Capsaicin 0.25% as Capsaicin palmitate

INDICATIONS AND USAGE

For the temporary relief of minor aches and pains of muscles and joints associated with arthritis, muscle strains, sprains, bruises, related muscle injuries, and simple backache. Provides penetrating pain relief.

WARNINGS

For external use only.

Do not apply to wounds and damaged skin.

When using this product use only as directed, temporary warming of skin may be experienced after application, avoid contact with eyes or mucous membranes, do not bandage tightly, do not expose the treated area to heat, and avoid activity that may cause perspiration.

Stop use and ask a doctor if condition worsens or if symptoms persist for more than 7 days or clear up and occur again within a few days.

KEEP OUT OF REACH OF CHILDREN

If swallowed, get medical help or contact a Poison Control Center right away.

DOSAGE AND ADMINISTRATION

Adults and children 18 years of age and older:

apply to affected areas not more than 3-4 times daily, rub in the cream until completely absorbed, the amount used depends on the depth of the pain, typically provides pain relief without any noticeable warming or cooling, wash hands thoroughly with soap and water after applying.

Children under 18 years of age: consult a doctor.

INACTIVE INGREDIENT

Butyrospermum parkii (shea) butter, ceteareth-20, cetyl alcohol, cocos nucifera (coconut) oil, ethylhexylglycerin, glycerin, glyceryl stearate, helianthus annuus (sunflower) seed oil, myristyl myristate, phenoxyethanol, polysorbate 20, stearic acid, water.